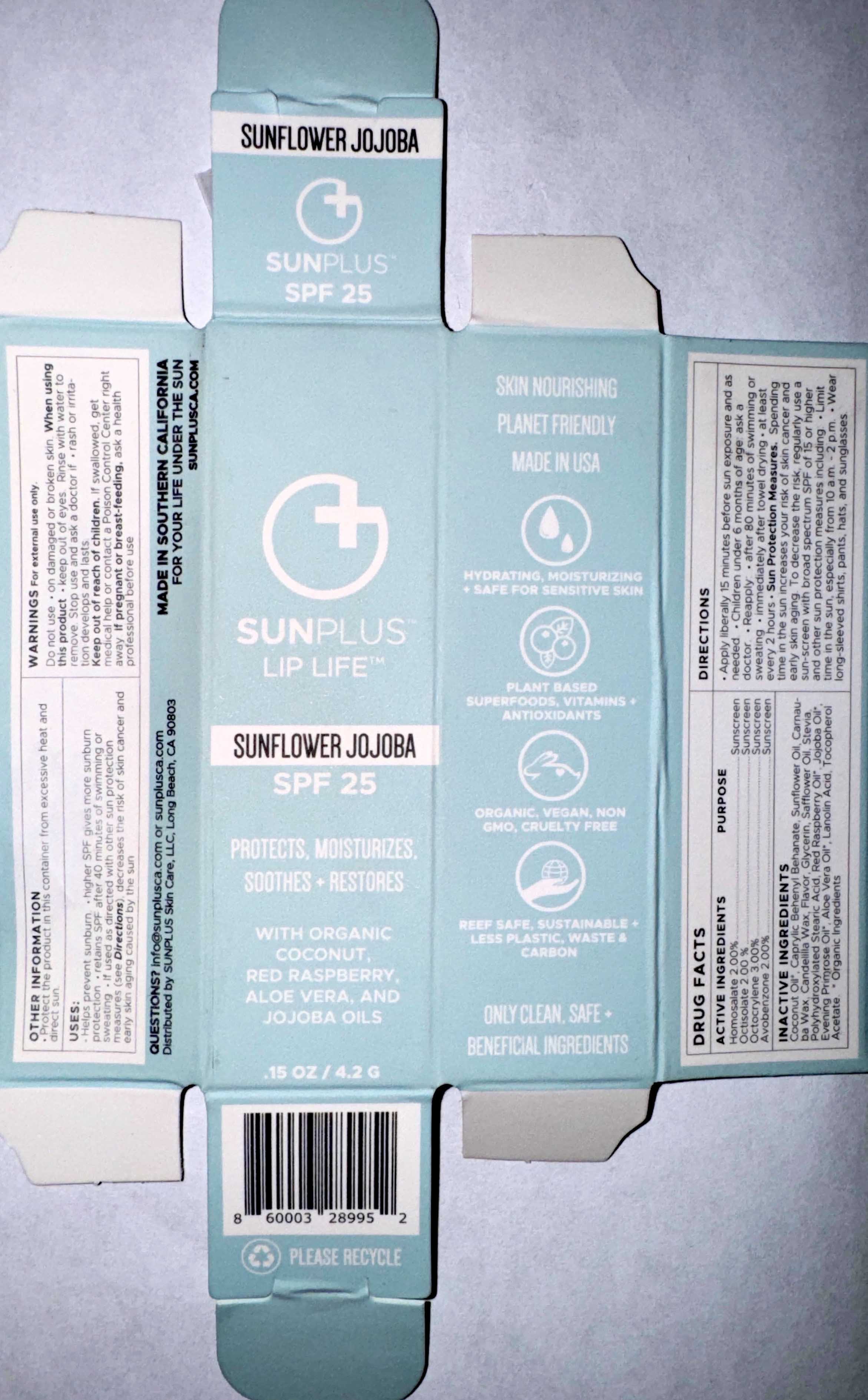 DRUG LABEL: SUNPLUS LIP LIFE
NDC: 65112-303 | Form: STICK
Manufacturer: I. Shay Cosmetics
Category: otc | Type: HUMAN OTC DRUG LABEL
Date: 20260209

ACTIVE INGREDIENTS: OCTOCRYLENE 0.03 g/4.2 g; OCTISALATE 0.02 g/4.2 g; AVOBENZONE 0.02 g/4.2 g; HOMOSALATE 0.02 g/4.2 g
INACTIVE INGREDIENTS: COCONUT OIL

ACTIVE INGREDIENT

Octocrylene 3%

Homosalate2%

Octisalate 2%

Avobenzone 2%

PURPOSE

Sunscreen protection

WARNING: Keep out of reach of children.

INDICATIONS AND USAGE

Helps prevent sunburn

Higher SFP gives more sunburn protection

Retains SPF after 40 minutes of swimming or sweating

If used as directed with other sun protection measures, decreases the risk of skin cancer and early skin aging caused by the Sun.

INACTIVE INGREDIENT

Coconut oil, Caprylic, BehenylBehenate, Sunflower oil, Carnauba Wax, Candelilla Wax, Flavor, Glycerin, Safflower oil, Stevia, PolyhydroxystearicAcid, Organic Raspberry oil, Organic Jojoba oil, Organic Evening primrose oil, Organic Aloe vera oil, Lanolin acid, Tocopherol Acetate.

Do not use on damaged or broken skin.

When using this product keep out of eyes.

Rinse with water to remove.

Stop use and ask a doctor if rash or irritation develops and lasts.

Keep out of reach of children.

If swallowed, get medical help or contact a Poison Control Center right away.

If pregnant or breastfeeding, ask a health professional before use.

DOSAGE AND ADMINISTRATION

Apply liberally 15 minutes before sun exposure and as needed. Children under 6 months of age: ask a doctor. Reapply after 80 minutes of swimming or sweating, immediately after towel drying, at least every 2 hours.

Sun Protection Measures: Spending time in the sun increases your risk of skin cancer and early skin aging. To decrease the risk, regularly use a sunscreen with broad spectrum SPF of 15 or higher and other sun protection measures including limit time in the sun, especially from 10am - 2pm, wear long-sleeved shirts, pants, hats, and sunglasses.